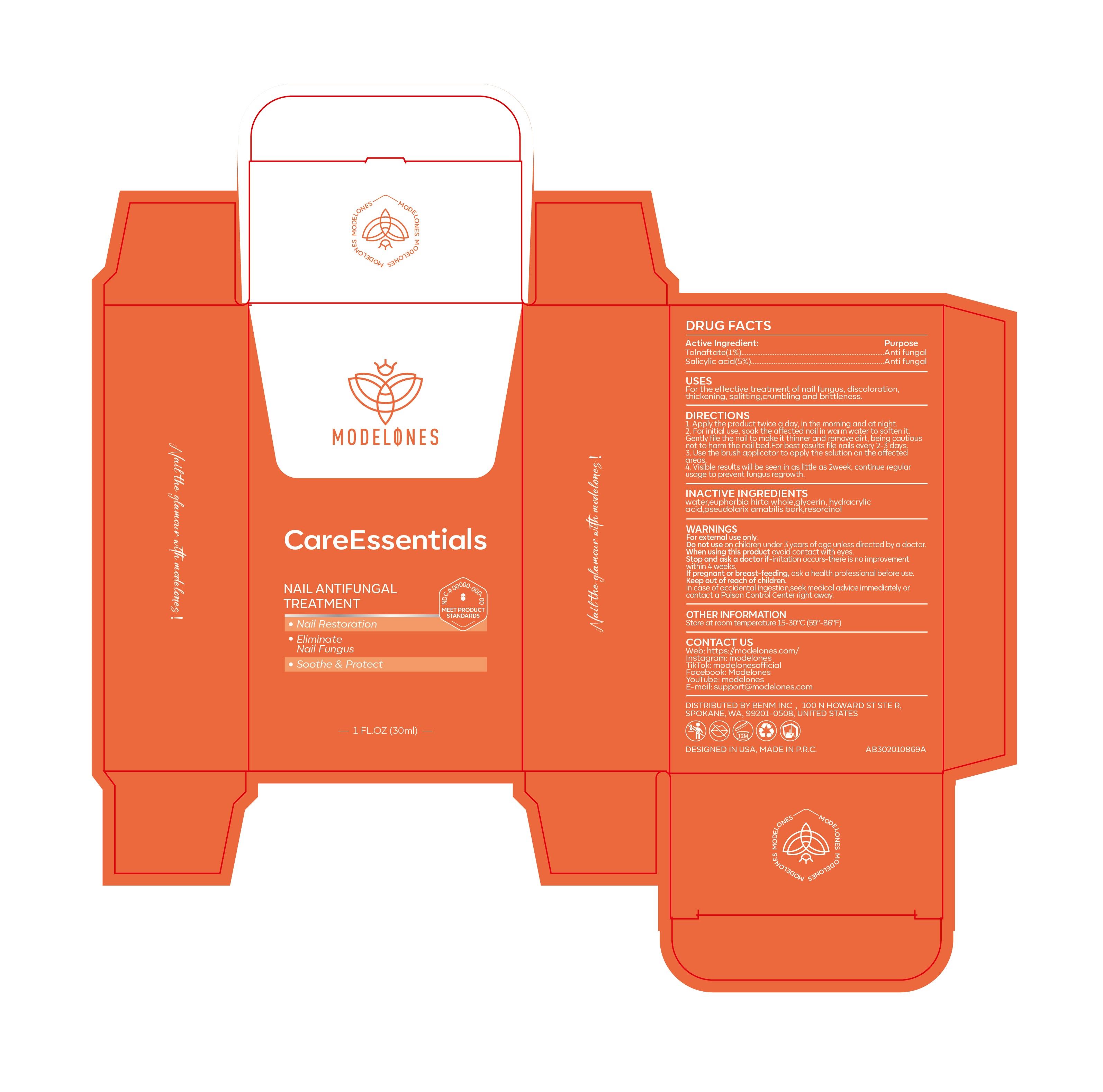 DRUG LABEL: Nail Antifungal Treatment
NDC: 85283-001 | Form: LIQUID
Manufacturer: BENM INC.
Category: otc | Type: HUMAN OTC DRUG LABEL
Date: 20260212

ACTIVE INGREDIENTS: SALICYLIC ACID 5 mg/100 mL; TOLNAFTATE 1 mg/100 mL
INACTIVE INGREDIENTS: WATER; GLYCERIN; PSEUDOLARIX AMABILIS BARK; HYDRACRYLIC ACID; EUPHORBIA HIRTA WHOLE; RESORCINOL

Nail Antifungal Treatment

PURPOSE

Anti fungal

ACTIVE INGREDIENT

Tolnaftate(1%)........................Anti fungal
Salicylic acid(5%) ........................Anti fungal

DIRECTIONS：
1. Apply the product twice a day, in the morning and at night.
2. For initial use, soak the affected nail in warm water to soften it. Gently file thenail to make it thinner and remove dirt, being cautious not to harm the nail bed.For best results file nails every 2-3 days.
3. Use the brush applicator to applythe solution on the affected areas.
4.Visible results will be seen in as little as 2week, continue regular usage toprevent fungus regrowth.

When using this product avoid contact with eyes.

Inactive ingredients：
water,euphorbia hirta whole,glycerin, hydracrylic acid,pseudolarix amabilis bark,resorcinol

Keep out of reach of children.
In case of accidental ingestion,seek medical advice immediately or contact a Poison Control Center right away.

Do not use on children under 3 years of age unless directed by a doctor.

OTHER INFORMATION
Store at room temperature 15-30°C (59°-86°F)

WARNINGS
For external use only.

Uses:
For the effective treatment of nail fungus, discoloration, thickening, splitting,crumbling and brittleness.

STOP USE

Stop and ask a doctor if-irritation occurs-there is no improvement
within 4 weeks.
If pregnant or breast-feeding, ask a health professional before use.
Keep out of reach of children.
In case of accidental ingestion,seek medical advice immediately or
contact a Poison Control Center right away.